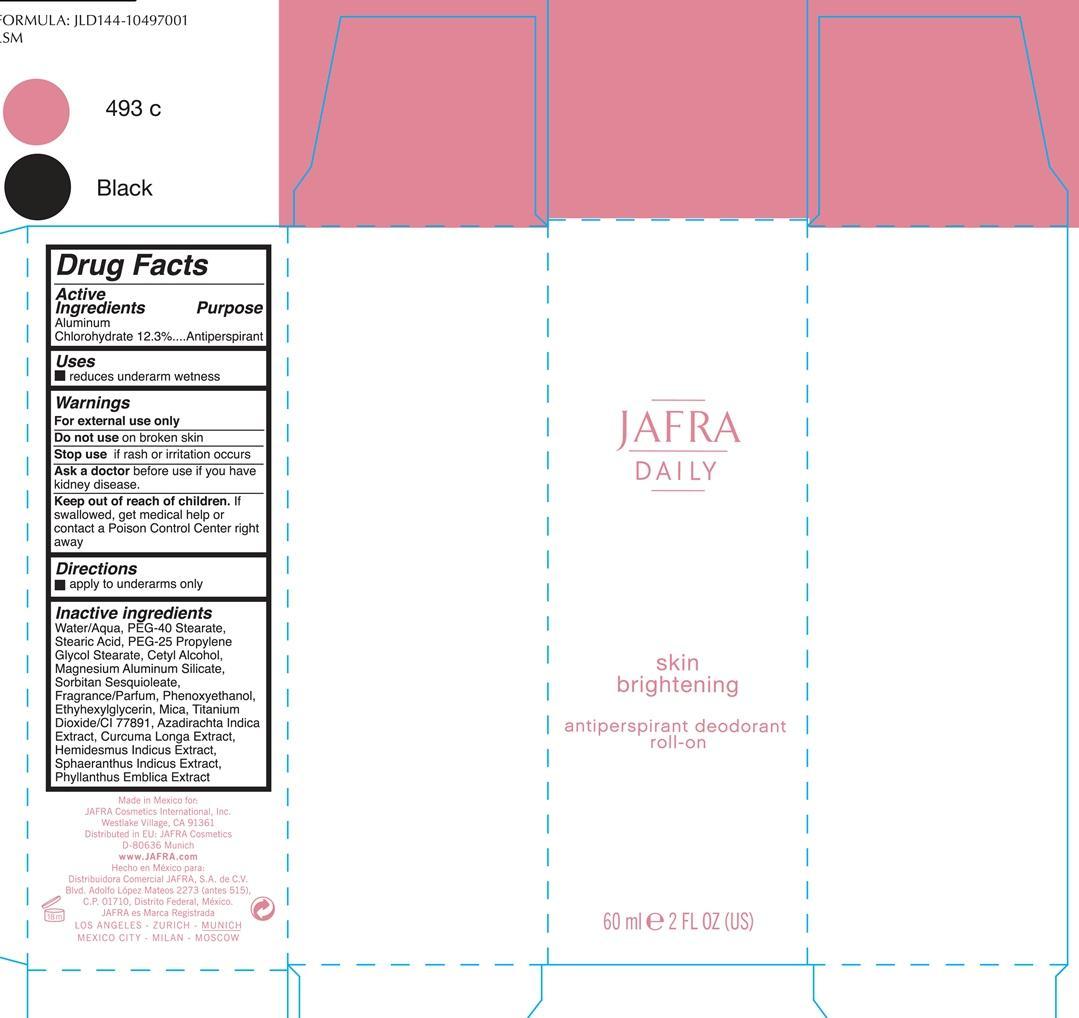 DRUG LABEL: Skin brightening antiperspirant deodorant roll-on
NDC: 68828-199 | Form: LIQUID
Manufacturer: Jafra cosmetics International
Category: otc | Type: HUMAN OTC DRUG LABEL
Date: 20190204

ACTIVE INGREDIENTS: ALUMINUM CHLOROHYDRATE 12.3 g/100 mL
INACTIVE INGREDIENTS: WATER; PEG-40 STEARATE; STEARIC ACID; PEG-25 PROPYLENE GLYCOL STEARATE; GLYCOL STEARATE; CETYL ALCOHOL; MAGNESIUM ALUMINUM SILICATE; SORBITAN SESQUIOLEATE; PHENOXYETHANOL; ETHYLHEXYLGLYCERIN; MICA; TITANIUM DIOXIDE; AZADIRACHTA INDICA BARK; TURMERIC; HEMIDESMUS INDICUS ROOT; SPHAERANTHUS INDICUS FLOWERING TOP; PHYLLANTHUS EMBLICA FRUIT

Jafra Daily Skin Brightening antiperspirant roll-on

Active ingredients Purpose

Aluminum Chlorohydrate 12.3% Antiperspirant

Uses

reduces underarm wetness

Keep out of reach of children. If swallowed, get medical help or contact a Poison Control Center right away.

Stop use if rash or irritation occurs

Warnings

For external use only

Do not use on broken skin

Ask a doctor before before use if you have kidney disease

Directions

Apply to underarms only

INACTIVE INGREDIENT

Water/Aqua, PEG-40 Stearate, PEG-25 Propylene Glycol Stearate, Cetyl Alcohol, Magnesium Aluminum Silicate, Sorbitan Sesquioleate, Fragrance/parfum, Phenoxyethanol, Ehtylhexylhexyl Glycerin, Mica, Titanium Dioxide/CI 77891, Azadirachta Indica Extract, Curcuma Longa, Hemisdesmus Indicus, Sphaeranthus Indicus Extract, Phyllanthus Emblica Extract

PACKAGE LABEL

Jafra

Daily

Skin Brightening

antiperspirant deodorant roll-on

60 ml 2 FL OZ